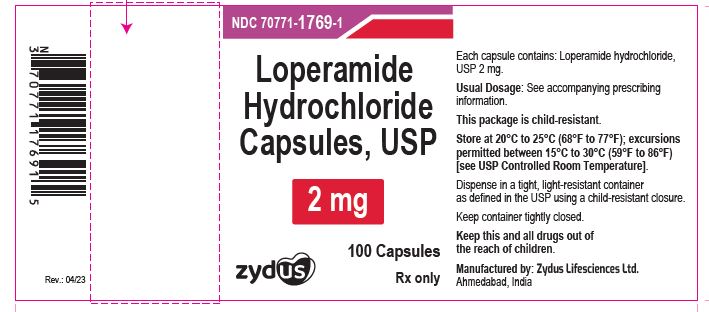 DRUG LABEL: Loperamide hydrochloride
NDC: 70771-1769 | Form: CAPSULE
Manufacturer: Zydus Lifesciences Limited
Category: prescription | Type: HUMAN PRESCRIPTION DRUG LABEL
Date: 20230619

ACTIVE INGREDIENTS: LOPERAMIDE HYDROCHLORIDE 2 mg/1 1
INACTIVE INGREDIENTS: FERRIC OXIDE RED; FERRIC OXIDE YELLOW; FERROSOFERRIC OXIDE; GELATIN; LACTOSE MONOHYDRATE; MAGNESIUM STEARATE; MICROCRYSTALLINE CELLULOSE 101; MICROCRYSTALLINE CELLULOSE 102; POTASSIUM HYDROXIDE; POVIDONE K30; SHELLAC; SILICON DIOXIDE; SODIUM LAURYL SULFATE; SODIUM STARCH GLYCOLATE TYPE A; TITANIUM DIOXIDE

Loperamide Hydrochloride Capsules, USP

PACKAGE LABEL.PRINCIPAL DISPLAY PANEL

Loperamide hydrochloride capsules USP, 2 mg

NDC 70771-1769-1

100 capsules

Rx only